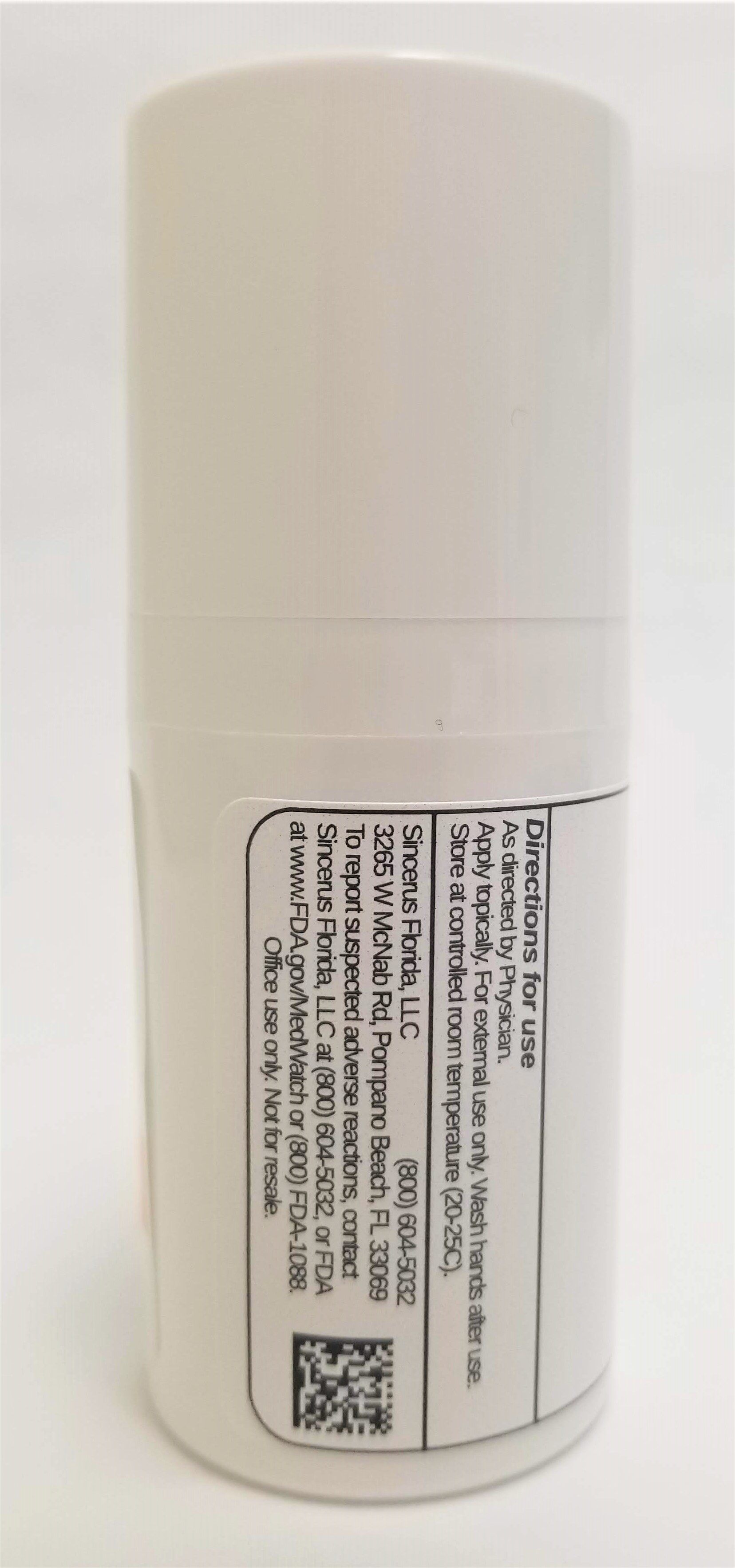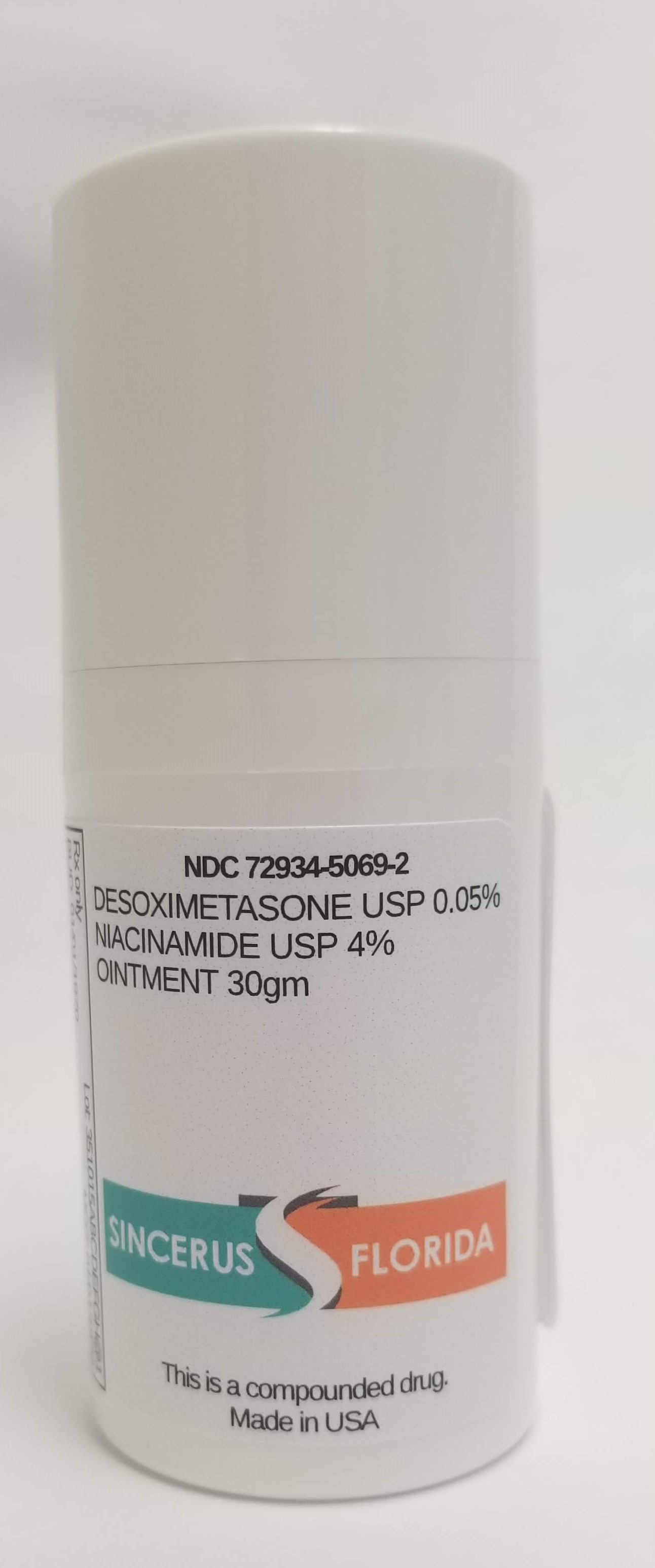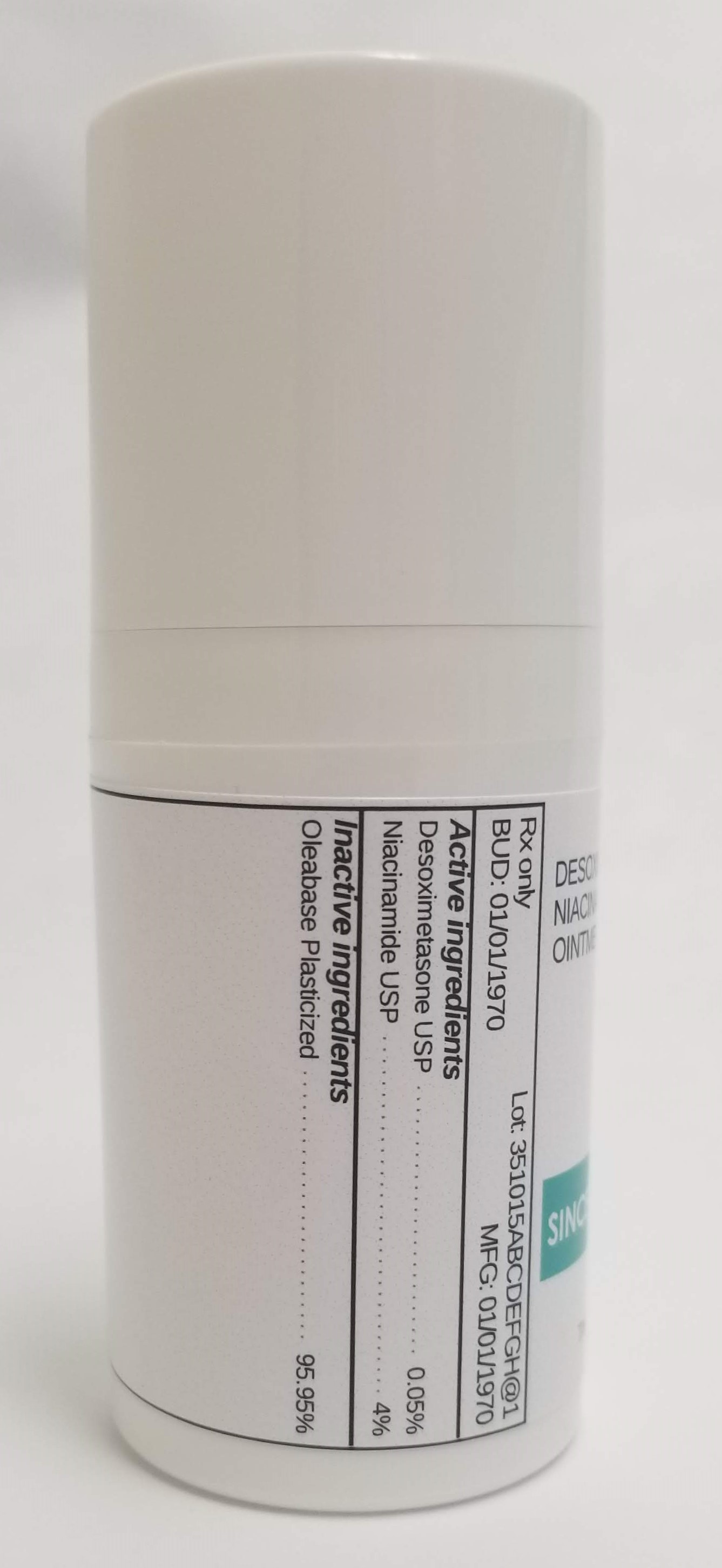 DRUG LABEL: DESOXIMETASONE 0.05% / NIACINAMIDE 4%
NDC: 72934-5069 | Form: OINTMENT
Manufacturer: Sincerus Florida, LLC
Category: prescription | Type: HUMAN PRESCRIPTION DRUG LABEL
Date: 20190522

ACTIVE INGREDIENTS: NIACINAMIDE 4 g/100 g; DESOXIMETASONE 0.05 g/100 g

DESOXIMETASONE 0.05% / NIACINAMIDE 4%